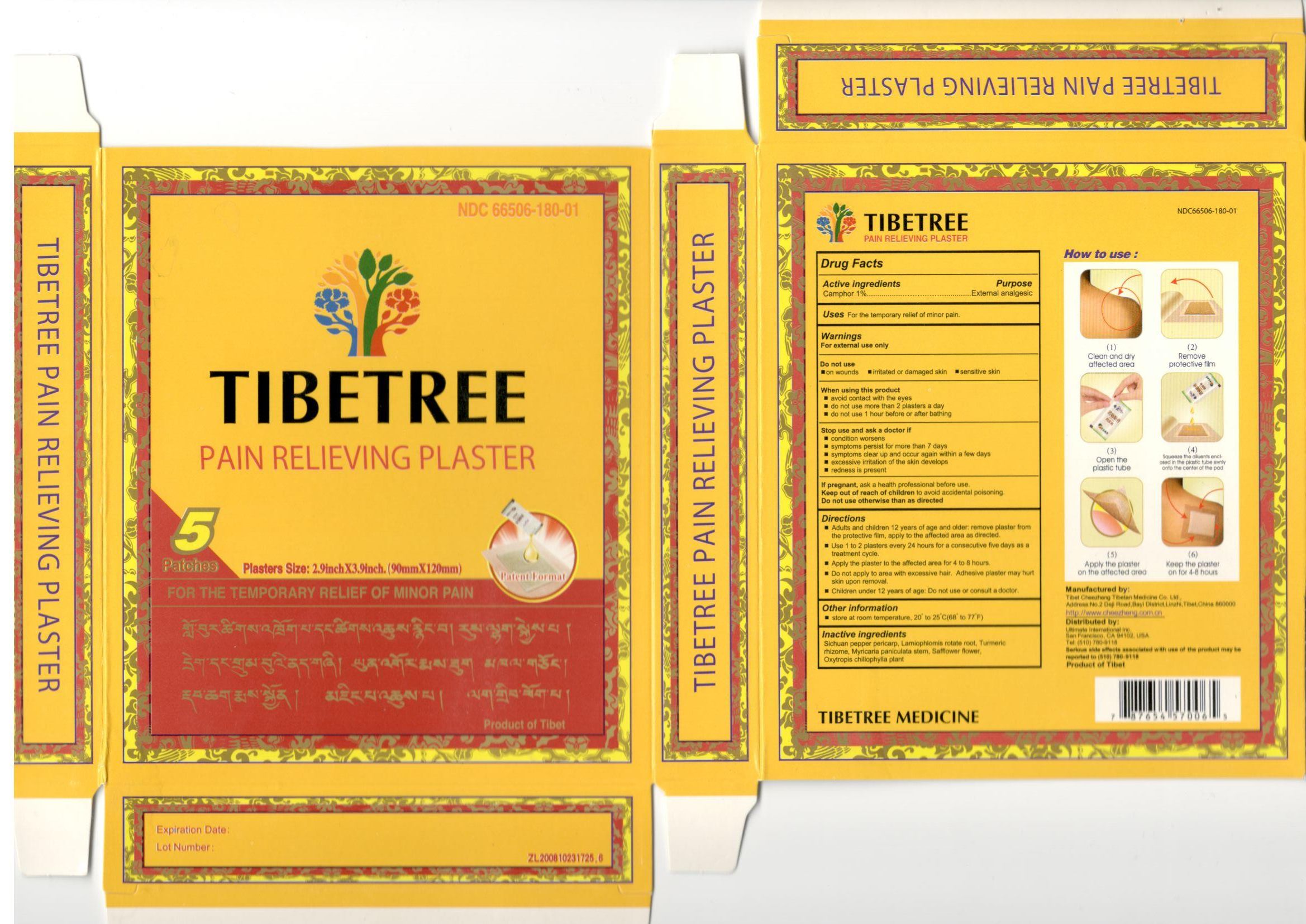 DRUG LABEL: Tibetree Pain Relieveing Plaster
NDC: 66506-180 | Form: PLASTER
Manufacturer: Tibet Cheezheng Tibetan Medicine Co. Ltd.
Category: otc | Type: HUMAN OTC DRUG LABEL
Date: 20190430

ACTIVE INGREDIENTS: CAMPHOR (NATURAL) 1 g/100 g
INACTIVE INGREDIENTS: ZANTHOXYLUM BUNGEANUM FRUIT RIND; CURCUMA LONGA WHOLE; CARTHAMUS TINCTORIUS FLOWER BUD; PHLOMOIDES ROTATA WHOLE; MYRICARIA PANICULATA STEM; OXYTROPIS CHILIOPHYLLA WHOLE

Tibetree Pain Relieveing Plaster

Active ingredients

Camphor 1%.................……….…….External analgesic

Do not use otherwise than as directed

Keep out of reach of children to avoid accidental poisoning

If pregnant

If pregnant, ask a health professional before use

Directions

- Adults and children 12 years of age and older: remove plaster from the protective film, apply to the affected area as directed.
- Use 1 to 2 plasters every 24 hours for a consecutive five days as a treatment cycle.
- Apply the plaster to the affected area for 4 to 8 hours.
- Do not apply to area with excessive hair. Adhesive plaster may hurt skin upon removal.
- Children under 12 years of age: Do not use or consult a doctor.

Other information

store at room temperature, 20° to 25°C(68° to 77F)

Inactive ingredients

Sichuan pepper pericarp, Lamiophlomis rotate root, Turmeric rhizome, Myricaria paniculata stem, Safflower flower, Oxytropis chiliophylla plant

Questions?

+1-510-780-9118

For external use only

Purpose

External analgesic

Do not use

- on wounds
- irritated or damaged skin
- sensitive skin

When using this product

- avoid contact with the eyes
- do not use more than 2 plasters a day
- do not use 1 hour before or after bathing

Stop use and ask a doctor if

- condition worsens
- symptoms persist for more than 7 days
- symptoms clear up and occur again within a few days
- excessive irritation of the skin develops
- redness is present

Warnings

For external use only

Uses

For the temporary relief of minor pain.

Tibetree 5 PDP.jpg